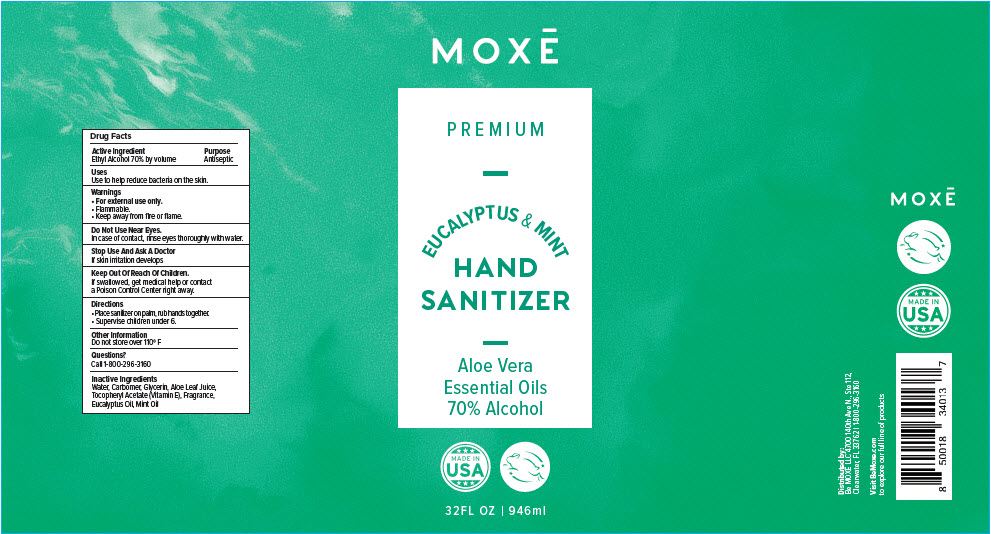 DRUG LABEL: MOXE Eucalyptus Mint Hand Sanitizer
NDC: 75435-814 | Form: GEL
Manufacturer: Be Moxe, LLC
Category: otc | Type: HUMAN OTC DRUG LABEL
Date: 20220208

ACTIVE INGREDIENTS: Alcohol 70 mL/100 mL
INACTIVE INGREDIENTS: Water; CARBOMER HOMOPOLYMER, UNSPECIFIED TYPE; Glycerin; Aloe; .ALPHA.-TOCOPHEROL ACETATE; Eucalyptus Oil

MOXĒ Eucalyptus Mint Hand Sanitizer

Drug Facts

Active Ingredient

Ethyl Alcohol 70% by volume

Purpose

Antiseptic

Uses

Use to help reduce bacteria on the skin.

Warnings

- For external use only.
- Flammable.
- Keep away from fire or flame.

Do Not Use Near Eyes.

In case of contact, rinse eyes thoroughly with water.

Stop Use And Ask A Doctor

If skin irritation develops

Keep Out Of Reach Of Children.

If swallowed, get medical help or contact a Poison Control Center right away.

Directions

- Place sanitizer on palm, rub hands together.
- Supervise children under 6.

Other Information

Do not store over 110° F

Questions?

Call 1-800-296-3160

Inactive Ingredients

Water, Carbomer, Glycerin, Aloe Leaf Juice, Tocopheryl Acetate (Vitamin E), Fragrance, Eucalyptus Oil, Mint Oil

Distributed by:
Be MOXĒ LLC 4700 140th Ave N., Ste 112,
Clearwater, FL 33762

PRINCIPAL DISPLAY PANEL - 946 ml Bottle Label

MOXĒ

PREMIUM

EUCALYPTUS & MINT

HAND
SANITIZER

Aloe Vera
Essential Oils
70% Alcohol

MADE IN
USA

32FL OZ | 946ml